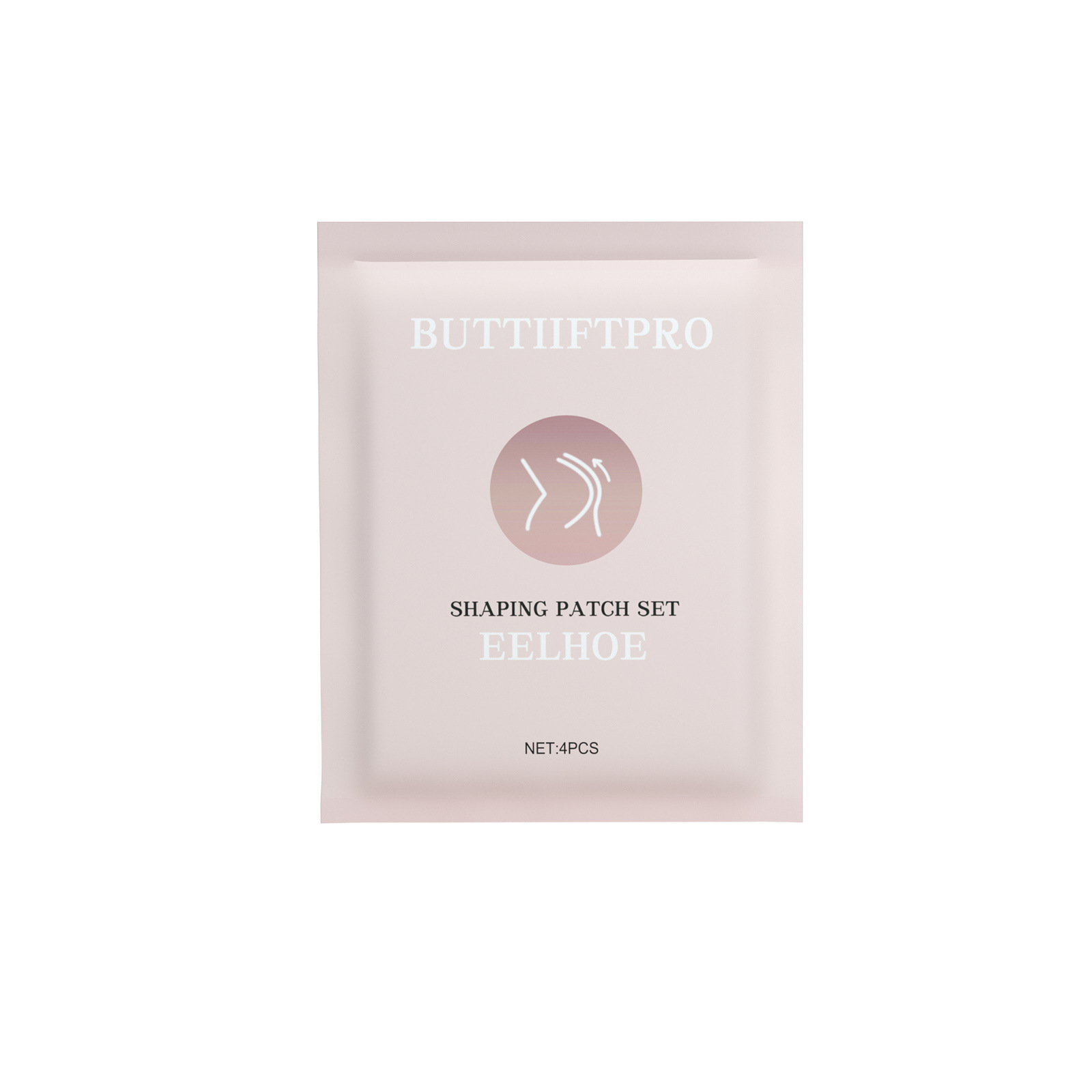 DRUG LABEL: Shaping Patch Set
NDC: 83675-015 | Form: PATCH
Manufacturer: Guangzhou Hanhai Trading Co., Ltd
Category: otc | Type: HUMAN OTC DRUG LABEL
Date: 20231007

ACTIVE INGREDIENTS: ALOE VERA LEAF 29 g/100 1
INACTIVE INGREDIENTS: GLYCERIN; CASTOR OIL; WATER

Active Ingredient

ALOE VERA LEAF JUICE 29.0%

Purpose

Slimming

Use

Eliminate edema
Tighten the arm
Slender and smooth

Warnings

For external use only. Do not take it internally.

Keep Out Of Reach Of Children
Sensitive Skin

Do not use

Product shall not be eat

When Using

Step 1
Clean and dry your buttbefore applying the patch.
Step 2
Peel off the plastic linerand apply it on your butt.Let it stay for 15 to 30 mins.
Step 3
Remove the patch andgently massage theremaining essence untilit is completely absorbed.

Stop Use

In case of adverse reactions, please stop using this product.If the symptoms.

Ask Doctor

ask doctor in case of Sensitive Skin

Keep Oot Of Reach Of Children

Keep Out Of Reach Of Children

Directions

Step 1
Clean and dry your buttbefore applying the patch.
Step 2
Peel off the plastic linerand apply it on your butt.Let it stay for 15 to 30 mins.
Step 3
Remove the patch andgently massage theremaining essence untilit is completely absorbed.

Other information

Store the product in a cool, dry and well-ventilated place

Avoid direct sunlight

Inactive ingredients

WATER
GLYCERIN
CASTOR OIL